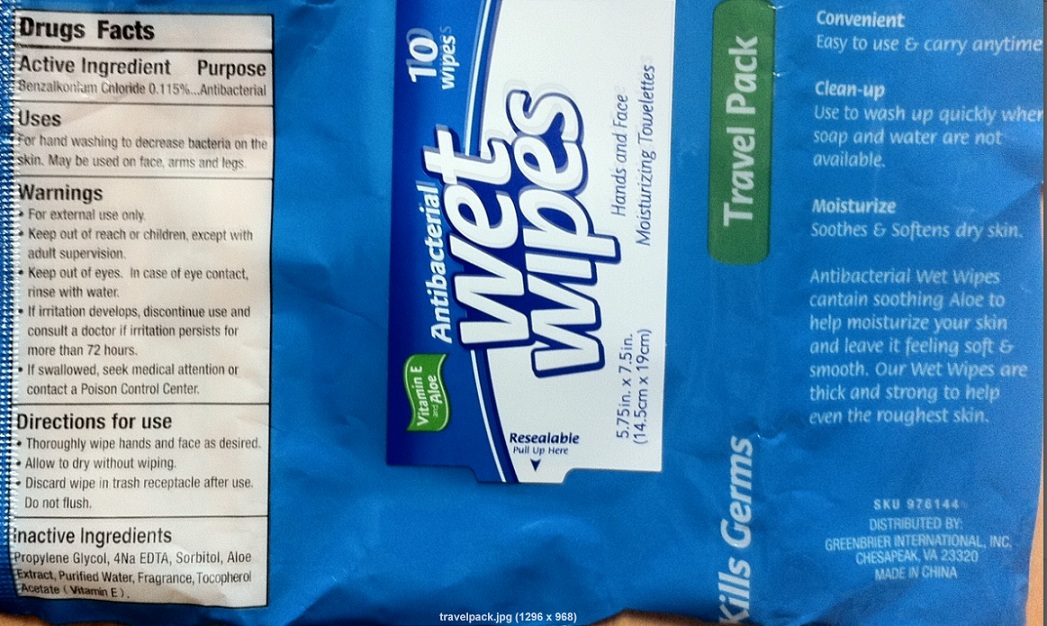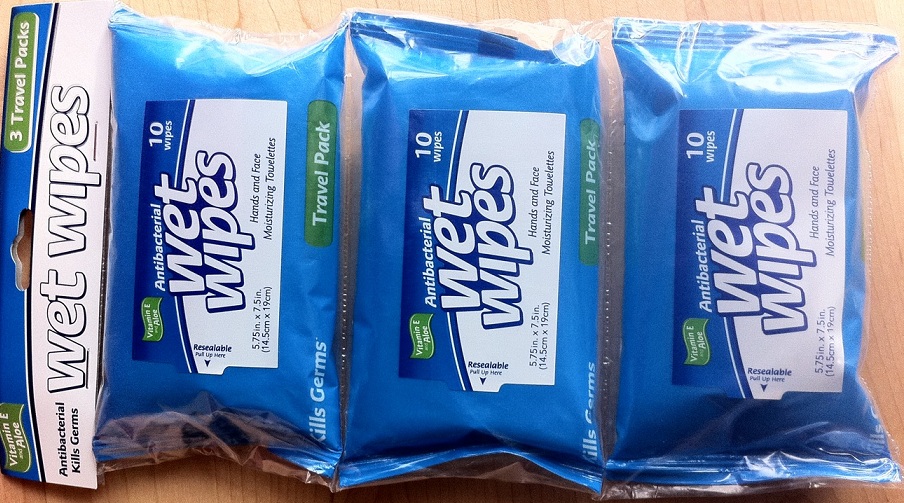 DRUG LABEL: ANTIBACTERIAL WET WIPES TRAVEL PACK
NDC: 40055-0614 | Form: SWAB
Manufacturer: Global Marketing Resources, Inc.
Category: otc | Type: HUMAN OTC DRUG LABEL
Date: 20101209

ACTIVE INGREDIENTS: BENZALKONIUM CHLORIDE 0.115 mL/100 mL
INACTIVE INGREDIENTS: PROPYLENE GLYCOL; EDETIC ACID; SORBITOL; ALOE; WATER; ALPHA-TOCOPHEROL ACETATE

Antibacterial Wet Wipes Hands and Face Moisturizing Towelettes with Vitamin E and Aloe

Active Ingredient

Benzalkonium chloride 0.115%

Purpose: Antibacterial

Uses

For hand washing to decrease bacterial on the skin. May be used on face arms and legs.

Warnings

For external use only

Keep out of eyes. In case of eye contact, rinse with water.

If irritation develops discontinue use and consult a doctor if irritation persists more than 72 hours

If swallowed, seek medical attention or contact a Poison Control Center.

KEEP OUT OF REACH OF CHILDREN

Keep out of the reach of children, except with adult supervision.

DOSAGE AND ADMINISTRATION

Direction for use:

Thoroughly wipe hands and face as desired.

Allow to dry without wiping.

Discard wipe in trash receptacle after use. Do not flush.

Inactive Ingredients

Propylene glycol, 4Na EDTA, Sorbitol, Aloe Extract, Purified Water, Fragrance, Tocopherol Acetate (Vitamin E).

PACKAGE LABEL

Convenient Easy to use and carry anytime!

Clean-Up Use to wash up quickly when soap and water are not available

Moisturize soothes and softens dry skin.

Antibacterial Wet Wipes contain soothing Aloe to help moisturize your skin and leave it feeling soft and smooth. Our Wet Wipes are thick and strong to help even the roughest skin.

Distributed by:

Greenbrier International, Inc.

Chesapeake, VA 23320

Made in China

Antibacterial Wet Wipes

Hands and Face Moisturizing Towelettes

with Aloe